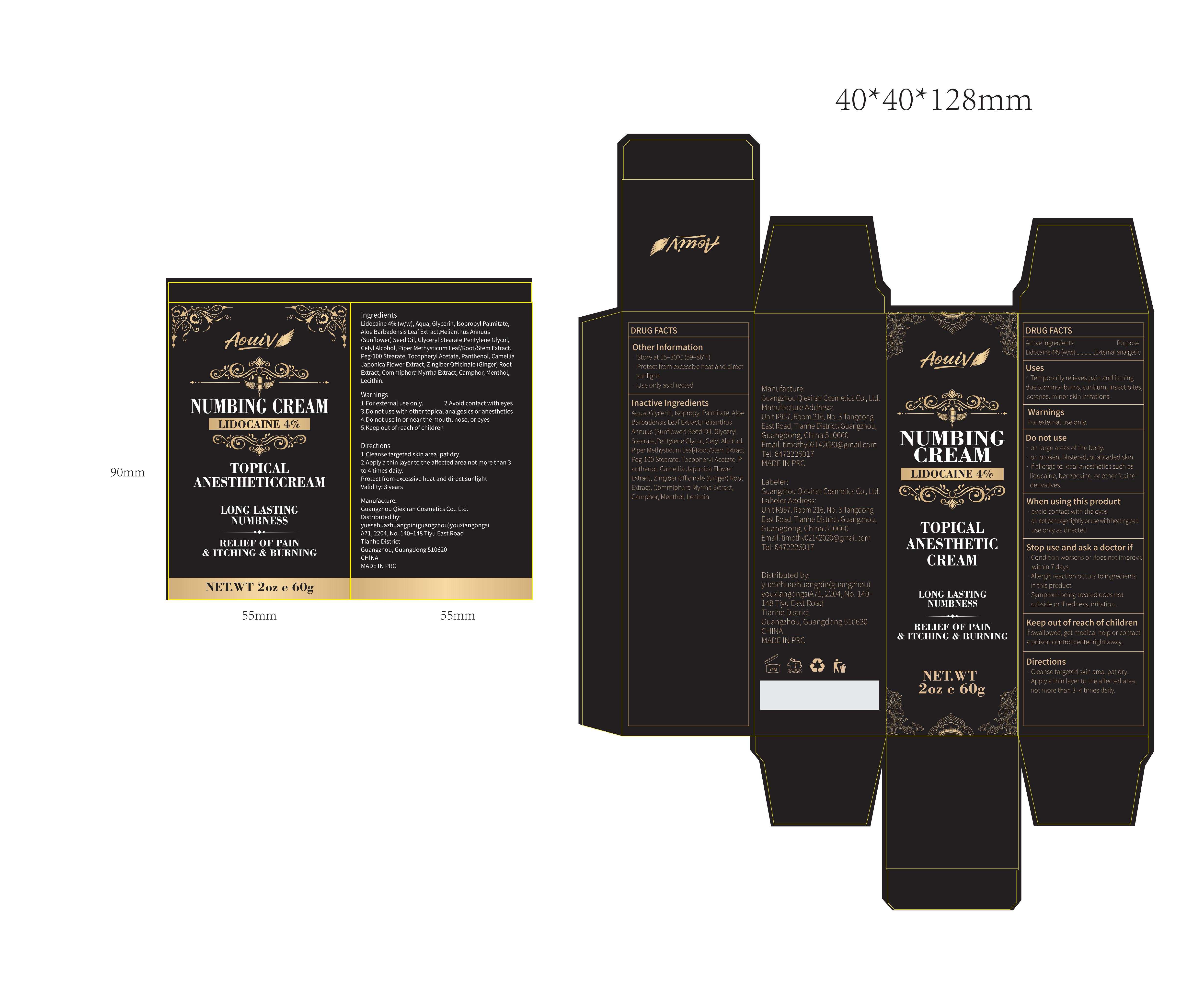 DRUG LABEL: Aouiv 4% Lidocaine Numbing Cream
NDC: 85817-003 | Form: CREAM
Manufacturer: Guangzhou Qiexiran Cosmetics Co., Ltd.
Category: otc | Type: HUMAN OTC DRUG LABEL
Date: 20250717

ACTIVE INGREDIENTS: LIDOCAINE 4 g/100 g
INACTIVE INGREDIENTS: ALOE BARBADENSIS LEAF; COMMIPHORA MYRRHA RESIN; HELIANTHUS ANNUUS (SUNFLOWER) SEED OIL; GLYCERIN; GINGER; ISOPROPYL PALMITATE; CAMELLIA JAPONICA FLOWER; CAMPHOR, (-)-; PENTYLENE GLYCOL; MACROPIPER METHYSTICUM WHOLE; ALPHA-TOCOPHEROL ACETATE; PEG-100 STEARATE; PIPER METHYSTICUM ROOT; AQUA; GLYCERYL STEARATE; MENTHOL; PANTHENOL; CETYL ALCOHOL

85817-003

Active Ingredient

Lidocaine 4% (w/w)

Purpose

External analgesic

Use

· Temporarily relieves pain and itching due to:

minor burns, sunburn, insect bites, scrapes, minor skin irritations.

Warnings

For external use only.

Do not use

· on large areas of the body.
· on broken, blistered, or abraded skin.
· if allergic to local anesthetics such as lidocaine, benzocaine, or other "caine" derivatives.

When Using

· avoid contact with the eyes
· do not bandage tightly or use with heating pad
· use only as directed

Stop Use

· Condition worsens or does not improve within 7 days.
·Allergic reaction occurs to ingredients in this product.
· Symptom being treated does not subside or if redness, irritation.

Ask Doctor

· Condition worsens or does not improve within 7 days.
·Allergic reaction occurs to ingredients in this product.
· Symptom being treated does not subside or if redness, irritation.

Keep Out Of Reach Of Children

If swallowed, get medical help or contact a poison control center right away.

Directions

· Cleanse targeted skin area, pat dry.
· Apply a thin layer to the affected area, not more than 3–4 times daily.

Other information

· Store at 15–30°C (59–86°F)
· Protect from excessive heat and direct sunlight
· Use only as directed

Inactive ingredients

Aqua, Glycerin, Isopropyl Palmitate, Aloe Barbadensis Leaf Extract,
Helianthus Annuus (Sunflower) Seed Oil, Glyceryl Stearate,
Pentylene Glycol, Cetyl Alcohol, Piper Methysticum Leaf/Root/Stem Extract, Peg-100 Stearate, Tocopheryl Acetate, Panthenol, Camellia Japonica Flower Extract,
Zingiber Officinale (Ginger) Root Extract, Commiphora Myrrha Extract, Camphor, Menthol, Lecithin.